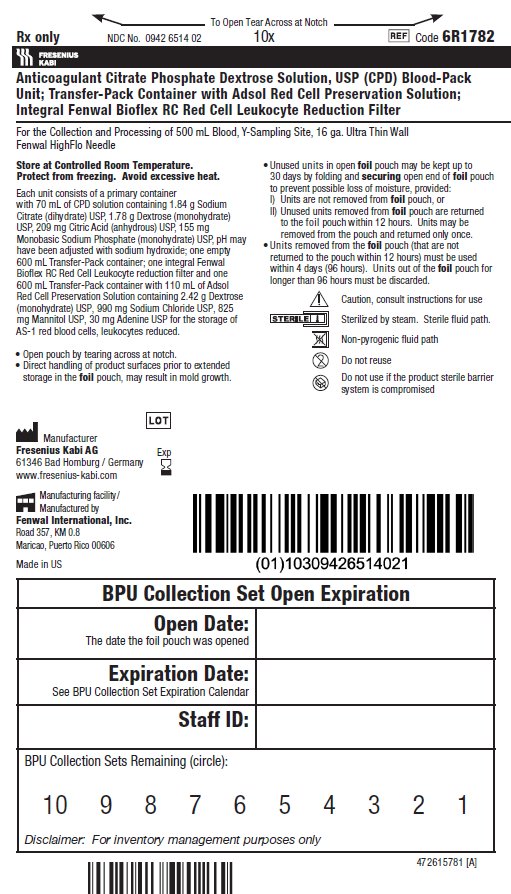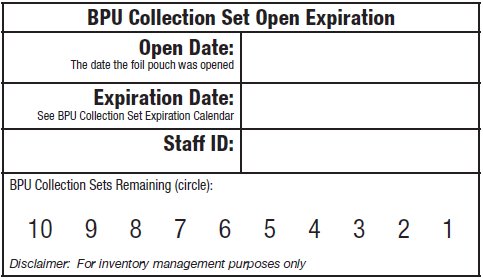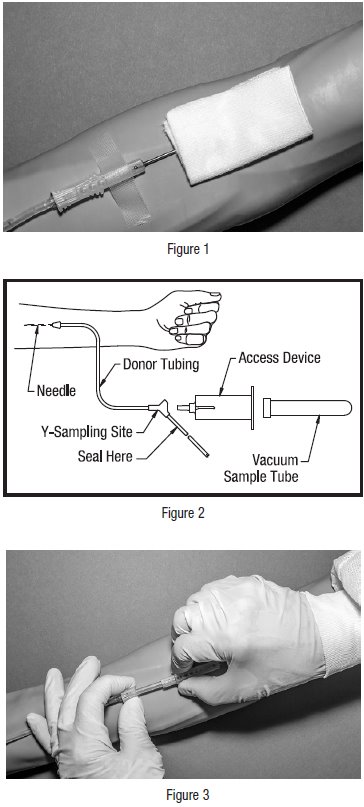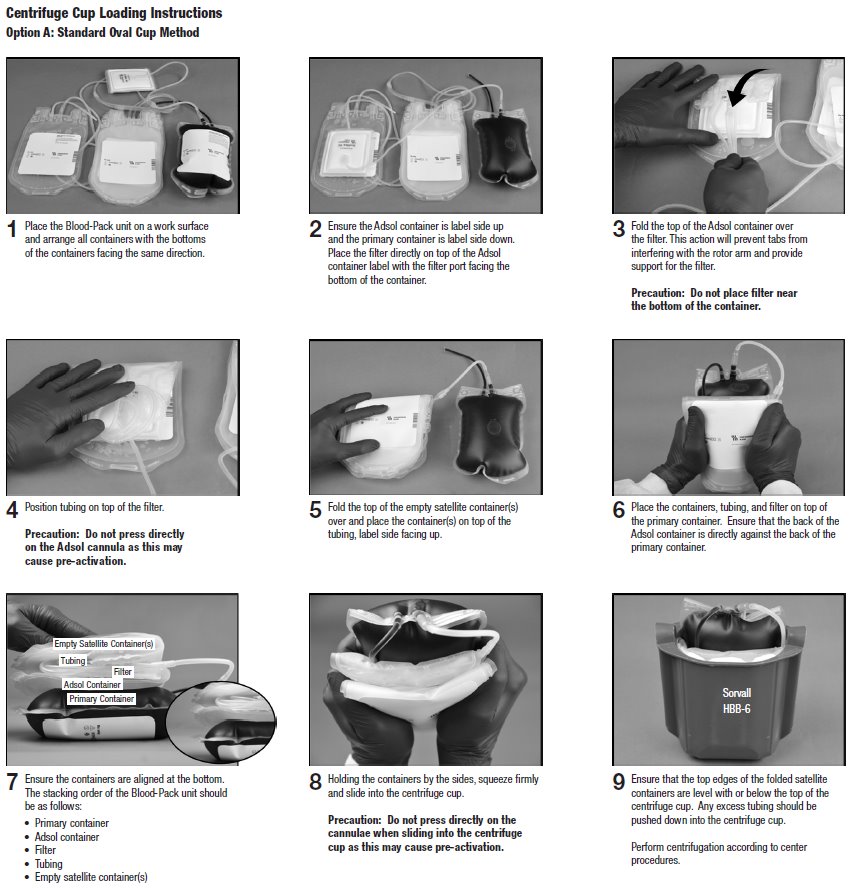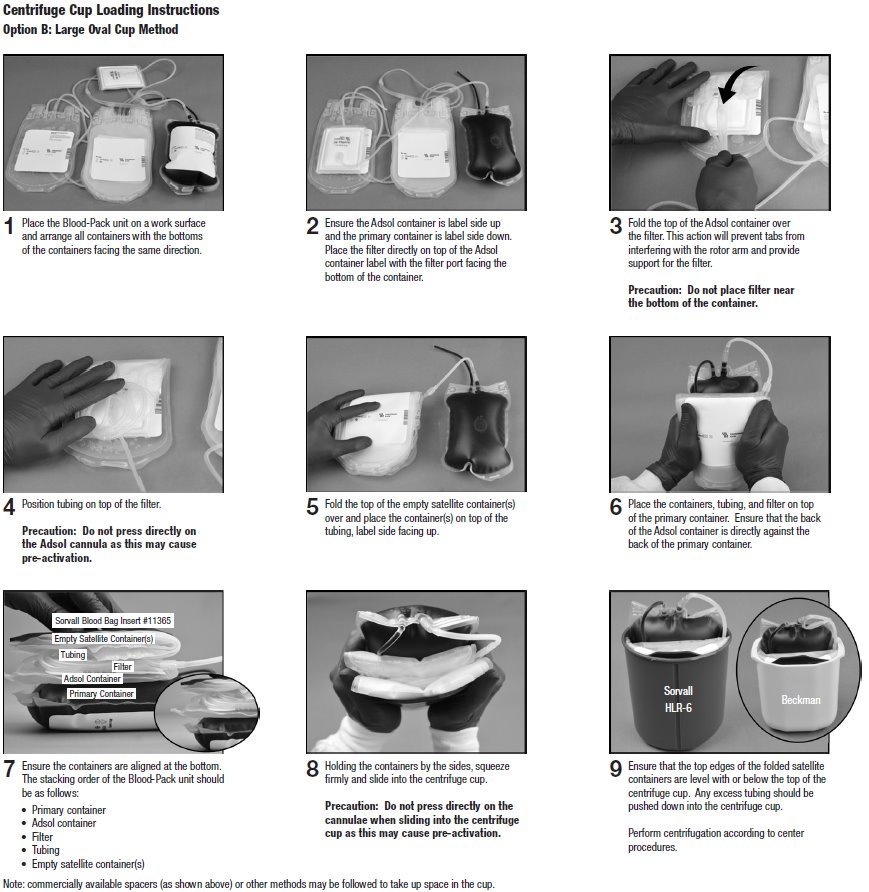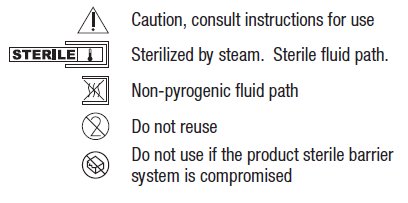 DRUG LABEL: ADSOL RED CELL PRESERVATION
NDC: 0942-6514 | Form: KIT | Route: INTRAVENOUS
Manufacturer: Fenwal, Inc.
Category: prescription | Type: HUMAN PRESCRIPTION DRUG LABEL
Date: 20221103

ACTIVE INGREDIENTS: TRISODIUM CITRATE DIHYDRATE 1.84 g/70 mL; DEXTROSE MONOHYDRATE 1.78 g/70 mL; ANHYDROUS CITRIC ACID 209 mg/70 mL; SODIUM PHOSPHATE, MONOBASIC, MONOHYDRATE 155 mg/70 mL; DEXTROSE MONOHYDRATE 2.42 g/110 mL; SODIUM CHLORIDE 990 mg/110 mL; MANNITOL 825 mg/110 mL; ADENINE 30 mg/110 mL
INACTIVE INGREDIENTS: SODIUM HYDROXIDE

Code 6R1782, 6R1784 20x Rx only
Fresenius Kabi

Blood-Pack Unit with an Integral Fenwal Bioflex RC Leukocyte Reduction Filter Using CPD/Adsol Red Cell Preservation Solution for Whole Blood Collection and Filtration of Red Blood Cells and Fenwal HighFlo Needle

Contains Y-Sampling Site for the collection of unanticoagulated whole blood samples for laboratory testing.

Store at Controlled Room Temperature. Protect from freezing. Avoid excessive heat.

Definition of "Controlled Room Temperature":

"A temperature maintained thermostatically that encompasses the usual and customary working environment of 20° to 25° C (68° to 77° F); that results in a mean kinetic temperature calculated to be not more than 25° C; and that allows for excursions between 15° C and 30° C (59° and 86° F) that are experienced in pharmacies, hospitals, and warehouses. Provided the mean kinetic temperature remains in the allowed range, transient spikes up to 40°C are permitted as long as they do not exceed 24 hours ... The mean kinetic temperature is a calculated value that may be used as an isothermal storage temperature that simulates the non isothermal effects of storage temperature variations."

Reference: United States Pharmacopeia, General Notices. United States Pharmacopeial Convention, Inc. 12601 Twinbrook Parkway, Rockville, MO.

Integral filter unit intended for leukocyte reduction of AS-1 red blood cells:

• At ambient temperature up to 8 hours after blood collection.

• At refrigerated temperature (1° to 6° C) up to 3 days after blood collection. If AS-1 red blood cells are prepared within 3 days after whole blood collection.

The leukocyte reduced red blood cells may then be stored for up to 42 days after collection.

Instructions for Use

Collection Procedure:

Use aseptic technique.

Notes:

- If the Y-Sampling Site is not used, donor samples may be collected using an alternative method following standard procedures.
- Nominal tubing dimensions of product are 0.118" inner diameter x 0.025" wall thickness.

Precautions:

- Upon removal of Blood-Pack unit from the clear plastic overwrap, visually inspect the unit.
- Do not use unless the solutions are clear.
- Before beginning procedure, obtain one access device for each Blood-Pack unit with Y-Sampling site to be processed.

1. Identify Blood-Pack unit using appropriate donor identification system.

2. Adjust donor scale to desired collection weight and position primary container on the donor scale as far as possible below donor arm.

3. Clamp donor tubing between Fenwal HighFlo^1 needle and primary container. (This step may be performed prior to step 1 or 2.)

4. Following blood center procedures, apply pressure to donor's arm and disinfect site of venipuncture.

5. Remove needle cover per instructions below:

a) Holding the hub and cover near the tamper-evident seal, twist cover and hub in opposite directions to break seal.
b) Remove needle cover, being careful not to drag the cover across the needle point.

6. Following blood center procedures, perform venipuncture, appropriately secure donor needle and/or tubing and release clamp on donor tubing. When good blood flow is established, stabilize the front of the needle guard to arm with tape (see Figure 1).

7. Mix blood and anticoagulant in the primary container immediately, at several intervals during collection, and immediately after collection.

8. Collect the appropriate volume based on Blood-Pack unit used.

Note: The volume of anticoagulant is sufficient for the blood collection indicated on Blood-Pack unit ± 10%.

9. Release the pressure on the donor's arm as appropriate.

Precaution: Do not proceed with the remaining steps until the entire whole blood unit is collected.

10. To avoid possible contamination of the whole blood unit, before filling whole blood sample tubes, hermetically seal the donor tubing near the Y-Sampling Site on the side leading to the primary container using a metal clip or appropriate alternate method.

Precaution: Complete steps 11 - 20 within approximately 4 minutes after sealing the donor tubing to avoid possible clot formation in the tubing.

11. To collect samples, insert the access device by pushing firmly into the Y-Sampling Site until the membrane seal is penetrated (see Figure 2).

Note: If the access device is assembled such that the outer barrel is screwed onto the Luer, make sure to rotate clockwise upon insertion to avoid barrel detaching from Luer.

12. Open the cap on the access device (if applicable).

13. Directly align the vacuum sample tube with the internal needle in the access device. Insert vacuum sample tube into device until the stopper is punctured.

14. Allow vacuum sample tube to fill with blood, then remove from the access device.

15. Repeat steps 13 and 14 until the desired number of vacuum sample tubes have been filled.

Notes:

- If the access device needs to be replaced, clamp the tubing between the needle and the Y-Sampling Site. Then, grasp base of Sampling Site with one hand and pull the access device out with the other hand. Firmly insert the new access device. Remove clamp and continue sampling.
- If the access device is assembled such that the outer barrel is screwed onto the Luer, make sure to rotate clockwise upon removal to avoid barrel detaching from Luer.
- The access device can only be replaced one time.

Precaution: When replacing the access device, be careful to avoid contact with any blood droplets on the Luer or Sampling Site. Discard used access device appropriately.

16. Release pressure on donor's arm.

17. If appropriate, apply clamp to donor tubing between needle and Y-Sampling Site.

18. Withdrawal of Needle (see Figure 3).

Precaution: The needle guard must be held stationary while the needle is withdrawn into it.

a) Place folded sterile gauze over puncture site and hold in place with finger tip without exerting pressure.
b) Hold sides of needle guard near the front, between the index finger and thumb. Pull the hub back smoothly until the needle is completely enclosed and securely locked into the needle guard.
c) Confirm the needle is completely enclosed and securely locked into the needle guard.

19. Remove and discard the Y-Sampling Site and needle guard into an appropriate biohazardous waste container following established procedures. If donor tubing is also to be discarded, hermetically seal donor tubing directly above the primary container and remove.

Note: Step 20 may be performed prior to step 19 if desired.

20. If the donor tubing is not hermetically sealed directly above the primary container, then strip the blood from the remaining donor tubing into the primary container and mix. If desired, allow tubing to refill.

Component Preparation:

Notes:

- If a platelet concentrate is to be prepared, it should be separated within 8 hours after blood collection.
- Fresh frozen plasma should be separated from the red blood cells and placed in the freezer at -18° C or colder within 8 hours after blood collection.
- Adsol red cell preservation solution should be added to the red blood cells immediately after the removal of plasma. Preparation of AS-1 red blood cells may vary depending on processing option selected:
a) Within 8 hours of blood collection if whole blood is held at ambient temperature.
b) Within 3 days of blood collection if whole blood is refrigerated.

21. At the appropriate time, prepare the Blood-Pack unit with integral filter for centrifugation.

22. Thoroughly mix the primary container end over end.

23. Load the Blood-Pack unit into a centrifuge cup per the instructions on page 3 or 4. Page 3 describes Option A, the method of centrifuge cup loading when using standard oval centrifuge cups. Page 4 describes Option B, the method of centrifuge cup loading when using large oval centrifuge cups. This method differs from Option A in steps 7 - 9 only and shows the use of a blood bag insert to help fill extra space inside the cup.

Notes:

- This guide is one method for centrifuge cup loading and applies to all Bioflex RC configurations. The specific stacking order and methods may vary depending on the workstation setup, centrifuge equipment, and your facilities Standard Operating Procedures.
- It is important to pack the filter properly in the centrifugation cup to avoid damage to the filter during centrifugation.
- Do not place the filter in the lower half of the centrifuge cup. See step 3 on page 3 or 4 for proper placement of filter.
- Do not press directly on the cannulae while performing any of the cup loading steps as this may cause pre-activation of the cannulae.

24. After loading the Blood-Pack unit into the centrifuge cup, perform centrifugation according to center procedures.

25. Following centrifugation, remove containers from the centrifuge cup taking care not to disturb the red blood cell/ plasma interface.

26. Place primary container in a plasma extractor and apply pressure. Clamp off tubing above the filter to prevent plasma flow into filter during plasma transfer. If applicable, clamp off tubing below Y-Junction leading to secondary Transfer Pack container not to be filled with plasma. Open the cannula on the top of the primary container to transfer plasma into the empty Transfer Pack container.

27. When the desired amount of plasma has been removed, clamp the tubing between the plasma container and the Y-connector closest to the plasma container and release pressure on the primary container. Seal and remove satellite container(s).

28. Position the Adsol red cell preservation solution container ensuring that the primary container remains below the level of the filter during prime. Open the cannula on the Adsol solution container and remove the clamp between the primary container and the filter. Transfer the Adsol through the filter into the primary container. Clamp the tubing between the filter and the primary container after prime is complete.

29. Mix the Adsol red cell preservation solution and red cells thoroughly.

Filtration Procedure:

Precaution: Red blood cell products collected from certain donors may have extended filtration times and the potential for ineffective filtration and leukoreduction.

30. Mix unfiltered AS-1 red blood cells thoroughly. Invert the unfiltered AS-1 red blood cells and hang the filter set such that the filter remains vertical. Filtration may be performed from 165 cm up to full length. To achieve maximum flow rate, allow the set to hang to full length. The storage container must remain below the level of the filter during filtration.

31. Filtration must be initiated up to 8 hours after collection at ambient condition or up to 3 days at refrigerated temperature.

32. Inspect all tubing to ensure It hangs freely without kinks.

33. Remove the clamp above the filter to start filtration.

Note: Manual or mechanical pressure should not be used to increase the flow rate through the filter. Tubing below the filter should not be stripped at any time during the filtration process.

Note: If filtration of red cells is initiated at ambient temperature, the filtration process can be completed at either ambient or refrigerated temperature prior to storing the red cells between 1 and 6° C. However, for optimal filtration time, it is recommended to complete the filtration at ambient temperature.

34. When filtration is complete, air can be observed in the inlet side of the filter. Hermetically seal and detach the tubing below the filter.

35. Make segments from the post filter tubing and leave segments attached to the filtered red cell storage container. (QC samples may be prepared by thoroughly mixing the filtered red cells and stripping this tubing prior to sealing the segments.)

36. Store the AS-1 red blood cells, leukocytes reduced between 1 and 6° C.

37. Infuse the red cells within 42 days of collection.

38. Quality control should be per FDA "Guidance for Industry - Pre-Storage Leukocyte Reduction of Whole Blood and Blood Components Intended for Transfusion", current issue.

Warning: Failure to achieve closed system processing conditions negates the extended storage claim and the red blood cell product must be transfused within 24 hours.

^1 Van der Meer, P.F., & de Korte, D. “Increase of blood donation speed by optimizing the needle-to-tubing connection: an application of donation software.” Vox Sanguinis 2009, 97:21-25.

©2021 Fresenius Kabi AG. All rights reserved.

All trademarks referred to are property of their respective owners.

Fresenius Kabi AG

61346 Bad Homburg / Germany

www.fresenius-kabi.com

1-800-933-6925

472315539 [A] 2021/09

PACKAGE LABEL.PRINCIPAL DISPLAY PANEL

To Open Tear Across at Notch

Rx only

NDC No. 0942 6514 02

10x

Code 6R1782

Fresenius Kabi

Anticoagulant Citrate Phosphate Dextrose Solution, USP (CPD) Blood-Pack Unit; Transfer-Pack Container with Adsol Red Cell Preservation Solution; Integral Fenwal Bioflex RC Red Cell Leukocyte Reduction Filter

For the Collection and Processing of 500 mL Blood, Y-Sampling Set, 16 ga. Ultra Thin Wall Fenwal HighFlo Needle

Store at Controlled Room Temperature.

Protect from freezing. Avoid excessive heat.

Each unit consists of a primary container with 70 mL of CPD solution containing 1.84 g Sodium

Citrate (dihydrate) USP, 1.78 g Dextrose (monohydrate) USP, 209 mg Citric Acid (anhydrous) USP, 155 mg Monobasic Sodium Phosphate (monohydrate) USP, pH may have been adjusted with sodium hydroxide; one empty 600 mL Transfer-Pack containers; one integral Fenwal Bioflex RC Red Cell Leukocyte reduction filter and one 600 mL Transfer-Pack container with 110 mL of Adsol Red Cell Preservation Solution containing 2.42 g Dextrose (monohydrate) USP, 990 mg Sodium Chloride USP, 825 mg Mannitol USP, 30 mg Adenine USP for the storage of AS-1 red blood cells, leukocytes reduced.

- Open pouch by tearing across at notch.
- Direct handling of product surfaces prior to extended storage in the foil pouch, may result in mold growth.
- Unused units in open foil pouch may be kept up to 30 days by folding and securing open end of foil pouch to prevent possible loss of moisture, provided:
I. Units are not removed from foil pouch, or
II. Unused units removed from foil pouch are returned to the foil pouch within 12 hours. Units may be removed from the pouch and returned only once.
- Units removed from the foil pouch (that are not returned to the pouch within 12 hours) must be used within 4 days (96 hours). Units out of the foil pouch for longer than 96 hours must be discarded.

Manufacturer

Fresenius Kabi AG

61346 Bad Homburg / Germany

www.fresenius-kabi.com

Manufacturing facility /

Manufactured by

Fenwal International, Inc.

Road 357, KM 0.8

Maricao, Puerto Rico 00606

Made in US

472615781 REV: A